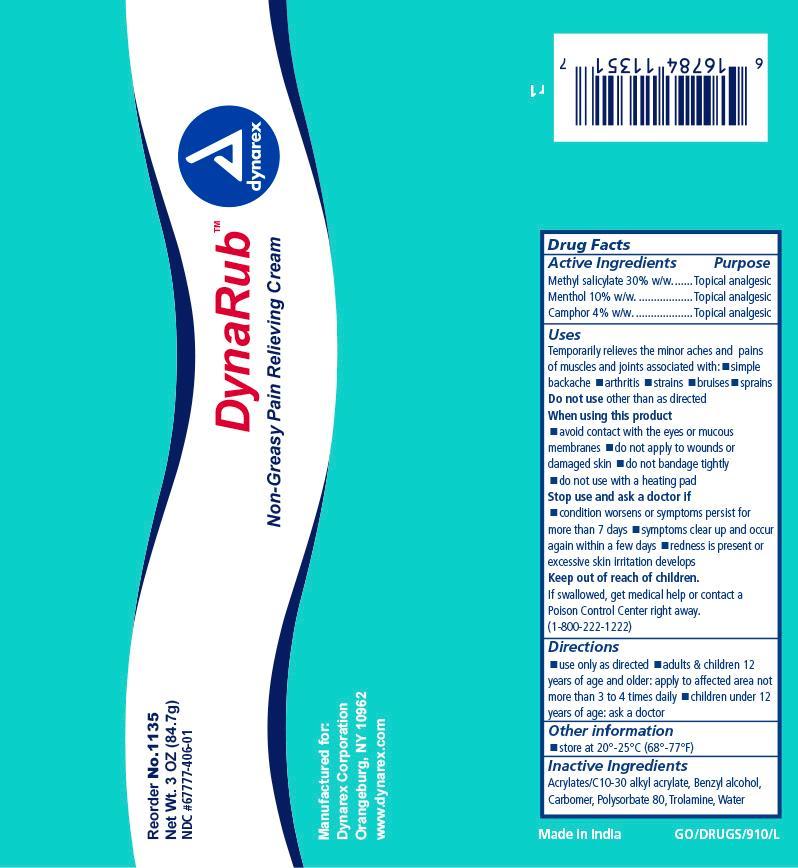 DRUG LABEL: Muscle rub
NDC: 67777-406 | Form: CREAM
Manufacturer: Dynarex Corporation
Category: otc | Type: HUMAN OTC DRUG LABEL
Date: 20150217

ACTIVE INGREDIENTS: MENTHOL 100 mg/1 g; CAMPHOR (NATURAL) 40 mg/1 g; METHYL SALICYLATE 300 mg/1 g
INACTIVE INGREDIENTS: CARBOMER HOMOPOLYMER TYPE C; TROLAMINE; (C10-C30)ALKYL METHACRYLATE ESTER; POLYSORBATE 80; BENZYL ALCOHOL; WATER

Dynarex Muscle Rub

Active Ingredient

Active Ingredient Purpose

Natural Menthol USP 10% Topical analgesic

Methyl salicylate 30% Topical analgesic

Camphor 4% Topical analgesic

Purpose

Temporary relief of minor aches and pains.

Indications and Usage

Uses

Temporary relief of minor aches and pains of sore muscles and joints associated with simple backache, arthritis, strains, bruises and sprains.

Warnings

For external use only.

- Avoid contact with the eyes or mucous membranes.
- Do not apply to wounds or damaged skin.
- Do not bandage tightly.
- Do not use with heating pad or device.

Stop Use

Stop Use And Ask A Doctor If:

- Condition worsens, or if symptoms persist for more than 7 days,
- symptoms clear up and occur again in a few days
- redness is present or excessive skin irritation develops

If pregnant or breast feeding:

Ask a health professional before use.

Keep Out Of Reach Of Children

If accidentally ingested, get medical help or contact a Poison Control Center immediately.

Dosage & Administration

Directions

- Use only as directed
- Adults and children 12 years of age and older: apply to the affected areas not more than 3 or 4 times daily.
- Children under 12 years of age: Consult a physician.

Other Information

Store at 20° - 25°C (68°-77°F)

Inactive Ingredients

Acrylates/C-10-30 Alkyl acrylate, benzyl alcohol, carbomer, polysorbate 80, trolamine, water.

Principle Display Panel

Dynarex Muscle Rub

dynarex mrub.jpg